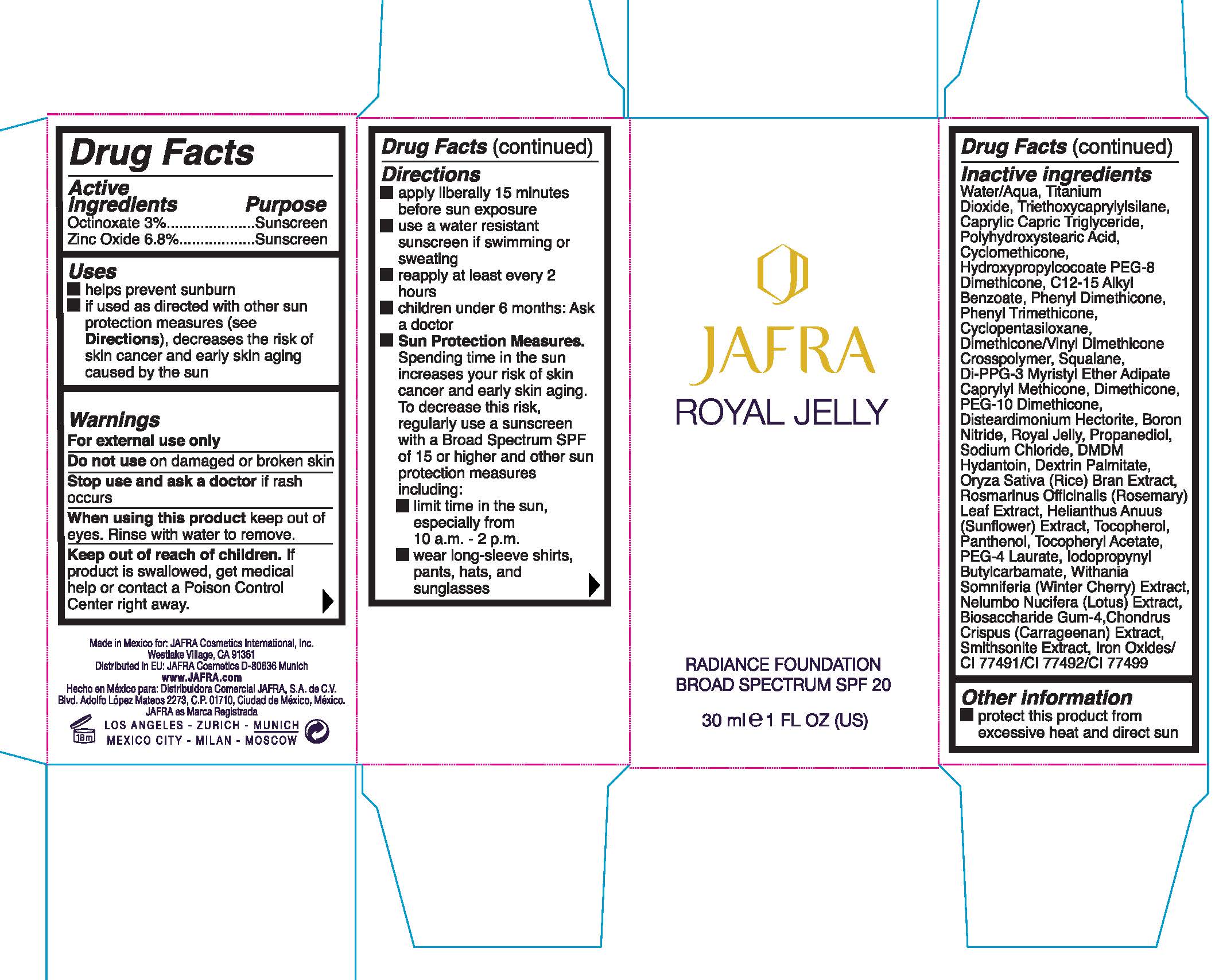 DRUG LABEL: Radiance Foundation Broad Spectrum SPF 20 - Nude
NDC: 68828-255 | Form: CREAM
Manufacturer: JAFRA COSMETICS INTERNATIONAL
Category: otc | Type: HUMAN OTC DRUG LABEL
Date: 20190617

ACTIVE INGREDIENTS: OCTINOXATE 3 g/100 mL; ZINC OXIDE 6.8 g/100 mL
INACTIVE INGREDIENTS: WATER; TITANIUM DIOXIDE; TRIETHOXYCAPRYLYLSILANE; POLYHYDROXYSTEARIC ACID (2300 MW); CYCLOMETHICONE; HYDROXYPROPYLCOCOATE PEG-8 DIMETHICONE; ALKYL (C12-15) BENZOATE; PHENYL TRIMETHICONE; CYCLOMETHICONE 5; DIMETHICONE/VINYL DIMETHICONE CROSSPOLYMER (SOFT PARTICLE); SQUALANE; DI-PPG-3 MYRISTYL ETHER ADIPATE; CAPRYLYL TRISILOXANE; DIMETHICONE; PEG-10 DIMETHICONE (600 CST); DISTEARDIMONIUM HECTORITE; BORON NITRIDE; ROYAL JELLY; PROPANEDIOL; SODIUM CHLORIDE; DMDM HYDANTOIN; RICE BRAN; ROSEMARY; HELIANTHUS ANNUUS FLOWERING TOP; TOCOPHEROL; PANTHENOL; .ALPHA.-TOCOPHEROL ACETATE; PEG-4 LAURATE; IODOPROPYNYL BUTYLCARBAMATE; BIOSACCHARIDE GUM-4; CHONDRUS CRISPUS CARRAGEENAN; FERRIC OXIDE RED; FERRIC OXIDE YELLOW; FERROSOFERRIC OXIDE

Nude - Radiance Foundation Broad Spectrum SPF 20

ACTIVE INGREDIENT

Octinoxate 3% .................. Sunscreen

Zinc Oxide 6.8% ................ Sunscreen

Uses

- helps prevent sunburn
- if used as directed with other sun protection measures (see Directions

Keep out of reach of children. If product is swallowed, get medical help or contact a Poison Control Center right away

Stop use and ask a doctor if rash occurs

Warnings

- For external use only
- Do not use on damaged or broken skin
- when using this product keep out of eyes. Rinse with water to remove

DOSAGE AND ADMINISTRATION

- apply liberally 15 minutes befor sun exposure
- use a water resistant sunscreen if swimming or sweating
- reapply at least every 2 hours
- children under 6 months: Ask a doctor
- Sun Protection Measures. Spending time in the sun increases your risk of skin cancer and early skin aging. To decrease the this risk, regularly use a sunscreen with a Broad Spectrum SPF 15 or higher and other sun protection measures including:
- limit time in the sun, especially from 10 a.m. - 2 p.m.
- wear long-sleev shirts, pants, hats, and sunglasses

INACTIVE INGREDIENT

Water/Aqua, Titanium Dioxide, Triethoxycaprylysilane, Caprylic Capric Triglyceride, Polyhydroxystearic Acid, Cyclomethicone, Hydroxypropylcocoate PEG-8 Diemthicone, C12-15 Alkyl Benzoate, Phenyl Dimethicone, Phenyl Trimethicone, Cyclopentasiloxane, Dimethicone/Vinyl Dimethicone Crosspolymer, Squalane, Di-PPG-3 Myristyl Ether Adipate Caprylyl Methicone, Dimethicone, PEG-10 Dimethicone, Disteardimonium Hectorite, Boron Nitride, Royal Jelly, Propanediol, Sodium Chloride, DMDM Hydantoin, Dextin Palmitate, Oryza Sativa (Rice) Bran Extract, Rosamarinus Officinalis (Rosemary) Leaf Extract, Helianthus Anuus (Sunflower) Extract, Tocopherol, Panthenol, Tocopheryl Acetate, PEG-4 Laurate, Iodopropynyl Butylcarbamate, Withania Somniferia (Winter Cherry) Extract, Nelumbo Nucifera (Lotus) Extract, Biosacchardie Gum-4, Chondrus Crispus (Carrageenan) Extract, Smithsonite Extract, Iron Oxides/CI 77491/CI 77492/CI 77499

PACKAGE LABEL

JAFRA

Royal Jelly

Raidiance Foundation

Broad Spectrum SPF 20

30 ml 1 FL OZ (US)